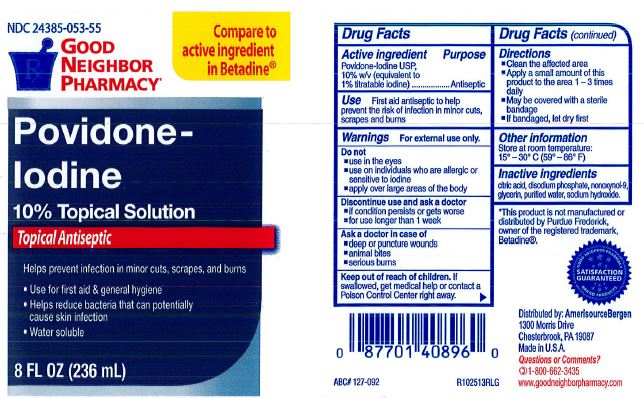 DRUG LABEL: Povidone Iodine
NDC: 24385-053 | Form: SOLUTION
Manufacturer: Amerisource Bergen
Category: otc | Type: HUMAN OTC DRUG LABEL
Date: 20231214

ACTIVE INGREDIENTS: POVIDONE-IODINE 0.1 g/1 mL
INACTIVE INGREDIENTS: CITRIC ACID MONOHYDRATE; GLYCERIN; SODIUM HYDROXIDE; WATER; SODIUM PHOSPHATE, DIBASIC; NONOXYNOL-9

GNP Povidone Iodine

ACTIVE INGREDIENT

Povidone Iodine,10% w/v (equivalent to 1% titratable iodine)

PURPOSE

Antiseptic

USE

First aid antiseptic to help prevent the risk of infection in minor cuts, scrapes and burns.

WARNINGS

For external use only.

Do not

- use in the eyes
- use on individuals who are allergic or sensitive to iodine
- apply over large areas of the body

Discontinue use and ask a doctor

- if condition persists or gets worse
- for use longer than 1 week

Ask a doctor in case of

- deep or puncture wounds
- animal bites
- serious burns

Keep out of reach of children

If swallowed, get medical help or contact a Poison Control Center right away.

DIRECTIONS

- Clean the affected area
- Apply a small amount of this product to the area 1-3 times daily
- May be covered with a sterile bandage
- If bandaged, let dry first

OTHER INFORMATION

Store at room temperature: 15° - 30° C (59° - 86° F)

INACTIVE INGREDIENTS

citric acid

dibasic sodium phosphate

nonoxynol-9

glycerin

purified water

sofium hydroxide

Questions

Questions or comments?

1-800-662-3435

www.goodneighborpharmacy.com

RECENT MAJOR CHANGES

Updated to match new label.